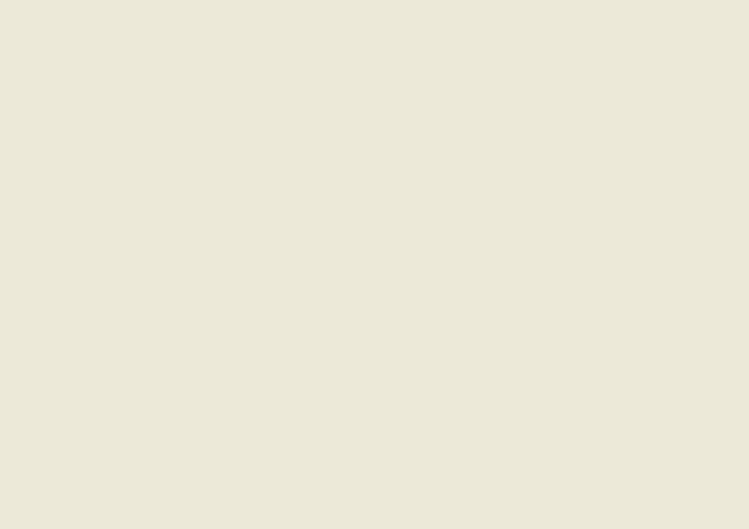 DRUG LABEL: USANA Lip Moisturizer
NDC: 63645-128 | Form: LIPSTICK
Manufacturer: Oralabs
Category: otc | Type: HUMAN OTC DRUG LABEL
Date: 20120423

ACTIVE INGREDIENTS: AVOBENZONE 3.0 g/1 1; OCTINOXATE 7.5 g/1 1; OCTISALATE 5.0 g/1 1
INACTIVE INGREDIENTS: COCONUT OIL 30 g/1 1; CASTOR OIL 23 g/1 1; WHITE WAX 27.5 g/1 1; COCOA BUTTER 0.001 g/1 1; SHEA BUTTER 0.001 g/1 1; .ALPHA.-TOCOPHEROL 1.998 g/1 1; PEAR JUICE 2.0 g/1 1

Drug Facts

Active ingredient

Avobenzone 3.0%

Octinoxate 7.5%

Octisalate 5.0%

Purpose

Sunscreen

Keep Out of Reach of Children

If swallowed, get medical help or contact a Poison Control Center right away.

Uses

Helps prevent sunburn. Help prevent and temporarily protect dry, chapped, or windburned lips if used as directed with other sun protection measures (see Directions), decreases the risk of skin cancer and early skin aging caused by the sun.

Warnings

For external use only. Do not use on damaged or broken skin. When using this product, keep out of eyes. Rinse with water to remove. Stop use and ask a doctor: if rash or irritation develops.

Directions

Apply liberally before sun exposure and as needed.

Sun Protection Measures: Spending time in the sun increases your risk of skin cancer and early skin aging. To decrease this risk, regularly use a sunscreen with a broad spectrum SPF or higher and other sun protection measures including: limiting time in the sun (especially from 10 a.m. - 2 p.m.) and wearing long-sleeve shirts, pants, hats, and sunglasses.

Children under 6 months of age: Ask a doctor before use.

Inactive ingredients

Cocos Nucifera (Coconut) Oil, Beeswax, Ricinus Communis (Castor) Seed Oil, Flavor, Tocopherol, Butyrospermum Parki (Shea) Butter, Theobroma Cacao (Cocoa) Seed Butter